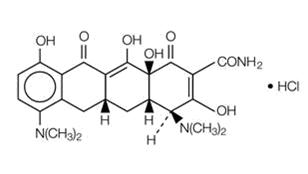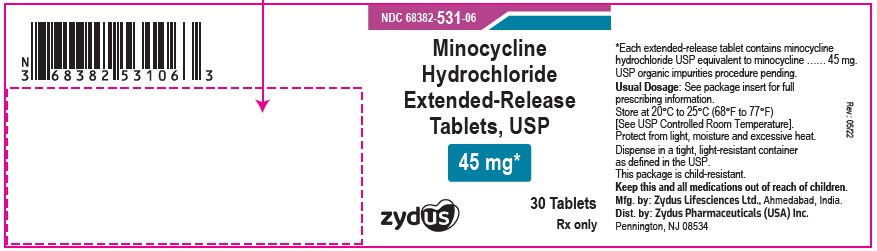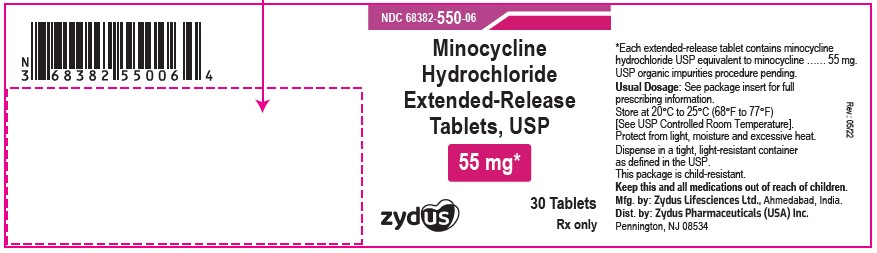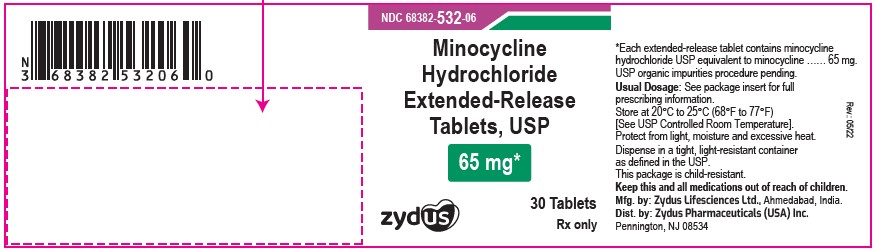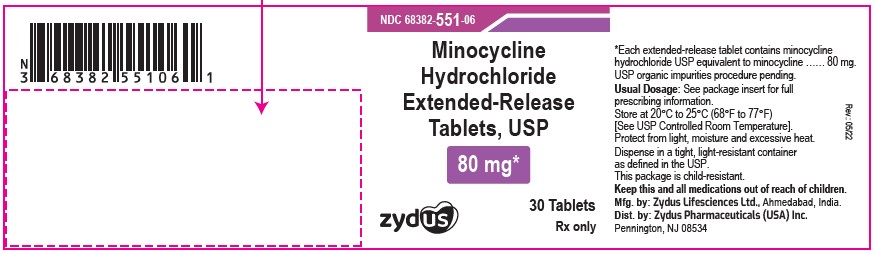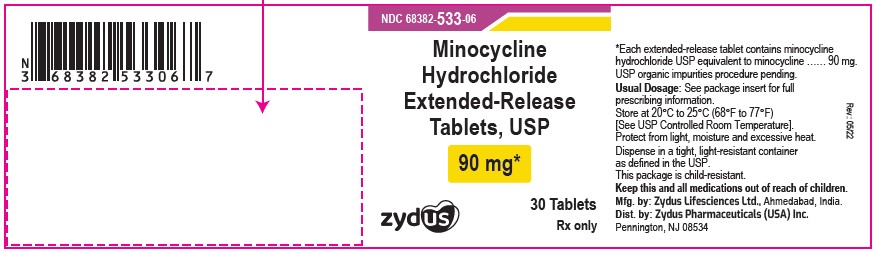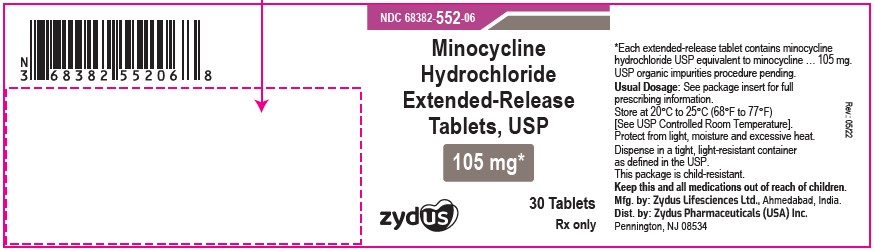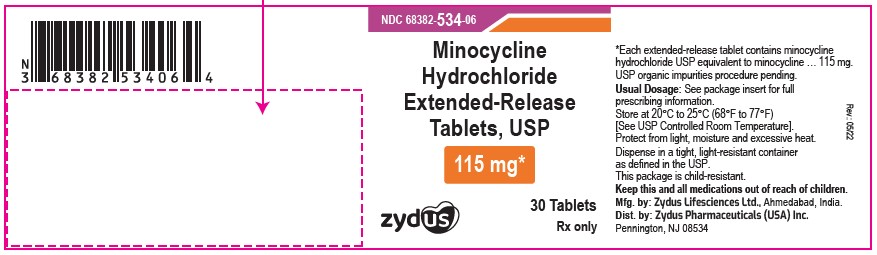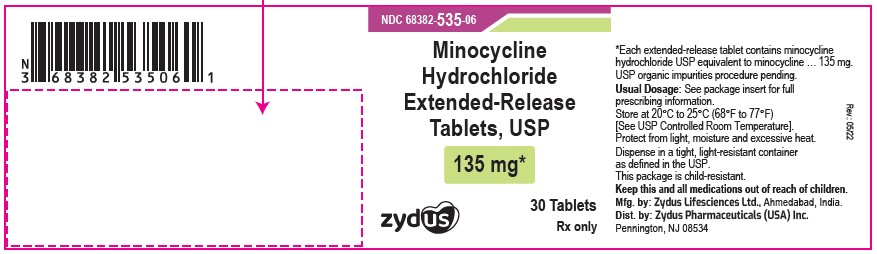 DRUG LABEL: minocycline hydrochloride
NDC: 68382-531 | Form: TABLET, EXTENDED RELEASE
Manufacturer: Zydus Pharmaceuticals (USA) Inc.
Category: prescription | Type: HUMAN PRESCRIPTION DRUG LABEL
Date: 20250605

ACTIVE INGREDIENTS: MINOCYCLINE HYDROCHLORIDE 45 mg/1 1
INACTIVE INGREDIENTS: FERRIC OXIDE YELLOW; FERROSOFERRIC OXIDE; HYPROMELLOSES; LACTOSE MONOHYDRATE; MAGNESIUM STEARATE; SILICON DIOXIDE; TITANIUM DIOXIDE; TRIACETIN

HIGHLIGHTS OF PRESCRIBING INFORMATION

These highlights do not include all the information needed to use MINOCYCLINE HYDROCHLORIDE EXTENDED-RELEASE TABLETS safely and effectively. See full prescribing information for MINOCYCLINE HYDROCHLORIDE EXTENDED-RELEASE TABLETS.
MINOCYCLINE HYDROCHLORIDE extended-release tablets, for oral use
Initial U.S. Approval: 1971

1 INDICATIONS AND USAGE

Minocycline hydrochloride extended-release tablets are a tetracycline-class drug indicated to treat inflammatory lesions of non-nodular moderate to severe acne vulgaris in patients 12 years of age and older. (1)

Limitations of Use

This formulation of minocycline has not been evaluated in the treatment of infections. To reduce the development of drug-resistant bacteria and to maintain the effectiveness of other antibacterial drugs, use minocycline hydrochloride extended-release tablets only as indicated. (1)

2 DOSAGE AND ADMINISTRATION

The recommended dosage of minocycline hydrochloride extended-release tablets are approximately 1 mg/kg once daily for 12 weeks. (2)

3 DOSAGE FORMS AND STRENGTHS

Extended-release tablets: 45 mg, 55 mg, 65 mg, 80 mg, 90 mg, 105 mg, 115 mg and 135 mg (3)

4 CONTRAINDICATIONS

Known hypersensitivity to any of the tetracyclines. (4)

5 WARNINGS AND PRECAUTIONS

- Serious Skin/Hypersensitivity Reactions:Minocycline has been associated with anaphylaxis, serious skin reactions, erythema multiforme, and drug rash with eosinophilia and systemic symptoms (DRESS) syndrome. Discontinue immediately if symptoms occur. (5.1)
- Tooth Discoloration and Enamel Hypoplasia:Use during the second and third trimesters of pregnancy, infancy, and childhood up to the age of 8years may cause permanent discoloration of the teeth (yellow-gray-brown). (5.2, 8.1, 8.4)
- Inhibition of Bone Growth:Use during the second and third trimesters of pregnancy, infancy, and childhood up to the age of 8 years may cause reversible inhibition of bone growth. (5.3, 8.1, 8.4)
- Clostridioides difficile-Associated Diarrhea (Antibiotic-Associated Colitis): Discontinue if Clostridioides difficile-associated diarrhea (antibiotic-associated colitis) occurs. (5.4)
- Hepatotoxicity: Discontinue if liver injury is suspected. (5.5)
- Central Nervous System Effects:May cause central nervous system side effects including light-headedness, dizziness, or vertigo. (5.6)
- Idiopathic Intracranial Hypertension: May cause idiopathic intracranial hypertension in adults and adolescents. Discontinue if symptoms occur. (5.7)
- Autoimmune Syndromes: Minocycline has been associated with autoimmune syndromes; discontinue immediately if symptoms occur. (5.8)
- Metabolic Effects: If renal impairment exists, reduce minocycline dosage. (5.9)

6 ADVERSE REACTIONS

The most commonly observed adverse reactions (incidence >5%) are headache, fatigue, dizziness, and pruritus. (6.1)

To report SUSPECTED ADVERSE REACTIONS, contact Zydus Pharmaceuticals (USA) Inc. at 1-877-993-8779 or FDA at 1-800-FDA-1088 or www.fda.gov/medwatch.

7 DRUG INTERACTIONS

Patients who are on anticoagulant therapy may require downward adjustment of their anticoagulant dosage. (7.1)

8 USE IN SPECIFIC POPULATIONS

Lactation: Breastfeeding is not recommended. (8.2)

FULL PRESCRIBING INFORMATION

1 INDICATIONS AND USAGE

Minocycline hydrochloride extended-release tablets are indicated to treat inflammatory lesions of non-nodular moderate to severe acne vulgaris in patients 12 years of age and older.

Limitations of Use

- Minocycline hydrochloride extended-release tablets did not demonstrate any effect on non-inflammatory acne lesions.
- This formulation of minocycline has not been evaluated in the treatment of infections [see Clinical Studies (14)].
- To reduce the development of drug-resistant bacteria as well as to maintain the effectiveness of other antibacterial drugs, use minocycline hydrochloride extended-release tablets only as indicated [see Warnings and Precautions (5.12)].

2 DOSAGE AND ADMINISTRATION

The recommended dosage of minocycline hydrochloride extended-release tablets is approximately 1 mg/kg once daily for 12 weeks. Table 1 provides the recommended minocycline hydrochloride extended-release tablets dosage based upon weight ranges.

Patient's Weight (kg) | Recommended Dosage (mg/day)
45 to 49 | 45
50 to 59 | 55
60 to 71 | 65
72 to 84 | 80
85 to 96 | 90
97 to 110 | 105
111 to 125 | 115
126 to 136 | 135

Higher dosages have not shown to be of additional benefit in the treatment of inflammatory lesions of acne and may be associated with more acute vestibular adverse reactions.

Swallow tablets whole. Do not chew, crush, or split the extended-release tablets.

Administer minocycline hydrochloride extended-release tablets with or without food [see Clinical Pharmacology (12.3)]. Ingestion of food along with minocycline hydrochloride extended-release tablets may help reduce the risk of esophageal irritation and ulceration.

In patients with renal impairment, decrease the daily dosage by either reducing the recommended individual doses and/or by extending the time intervals between doses [see Warnings and Precautions (5.9)].

3 DOSAGE FORMS AND STRENGTHS

- 45 mg extended-release tablets are grey colored, modified capsule shaped, biconvex, coated tablets, debossed with "531" on one side and plain on other side.
- 55 mg extended-release tablets are yellow colored, modified capsule shaped, biconvex, coated tablets, debossed with "550" on one side and plain on other side.
- 65 mg extended-release tablets are blue colored, modified capsule shaped, biconvex, coated tablets, debossed with "532" on one side and plain on other side.
- 80 mg extended-release tablets are whitish blue colored, modified capsule shaped, biconvex, coated tablets, debossed with "551" on one side and plain on other side.
- 90 mg extended-release tablets are light yellow colored, modified capsule shaped, biconvex, coated tablets, debossed with "533" on one side and plain on other side.
- 105 mg extended-release tablets are light blue colored, modified capsule shaped, biconvex, coated tablets, debossed with "552" on one side and plain on other side.
- 115 mg extended-release tablets are green colored, modified capsule shaped, biconvex, coated tablets, debossed with "534" on one side and plain on other side.
- 135 mg extended-release tablets are light pink colored, modified capsule shaped, biconvex, coated tablets, debossed with "535" on one side and plain on other side.

4 CONTRAINDICATIONS

Minocycline hydrochloride extended-release tablet is contraindicated in patients with history of a hypersensitivity reaction to any of the tetracyclines [see Warnings and Precautions (5.1)].

5 WARNINGS AND PRECAUTIONS

5.1 Serious Skin/Hypersensitivity Reactions

Cases of anaphylaxis, serious skin reactions (e.g., Stevens-Johnson syndrome), erythema multiforme, and drug rash with eosinophilia and systemic symptoms (DRESS) syndrome have been reported postmarketing with minocycline use in patients with acne. DRESS syndrome consists of cutaneous reaction (such as rash or exfoliative dermatitis), eosinophilia, and one or more of the following visceral complications such as: hepatitis, pneumonitis, nephritis, myocarditis, and pericarditis. Fever and lymphadenopathy may be present. In some cases, death has been reported. If this syndrome is recognized, discontinue minocycline immediately.

5.2 Tooth Discoloration and Enamel Hypoplasia

The use of tetracycline-class drugs, including minocycline, during tooth development (second and third trimesters of pregnancy, infancy, and childhood up to the age of 8 years) may cause permanent discoloration of the teeth (yellow-gray -brown). Permanent discoloration of the teeth is more common during long-term use of tetracycline-class drugs but has been observed following repeated short-term courses. Enamel hypoplasia has also been reported. Use of minocycline is not recommended during tooth development.

Advise the patient of the potential risk to the fetus if minocycline is used during the second or third trimester of pregnancy [see Use in Specific Populations (8.1, 8.4)].

5.3 Inhibition of Bone Growth

The use of tetracycline-class drugs, including minocycline, during the second and third trimesters of pregnancy, infancy, and childhood up to the age of 8 years may cause reversible inhibition of bone growth. All tetracyclines, including minocycline, form a stable calcium complex in any bone-forming tissue. A decrease in fibula growth rate has been observed in premature human infants given oral tetracycline in doses of 25 mg/kg every 6 hours. This reaction was shown to be reversible when the drug was discontinued.

Advise the patient of the potential risk to the fetus if minocycline is used during the second or third trimester of pregnancy [see Use in Specific Populations (8.1, 8.4)].

5.4 Clostridioides difficile-Associated Diarrhea (Antibiotic-Associated Colitis)

Clostridioides difficile-associated diarrhea (CDAD) has been reported with nearly all antibacterial agents, including minocycline, and may range in severity from mild diarrhea to fatal colitis.

C. difficile produces toxins A and B which contribute to the development of CDAD. Hypertoxin-producing strains of C. difficile cause increased morbidity and mortality, as these infections can be refractory to antimicrobial therapy and may require colectomy. CDAD must be considered in all patients who present with diarrhea following antibiotic use. Careful medical history is necessary since CDAD has been reported to occur over two months after the administration of antibacterial agents.

If CDAD is suspected or confirmed, discontinue minocycline.

5.5 Hepatotoxicity

Postmarketing cases of serious liver injury, including irreversible drug-induced hepatitis and fulminant hepatic failure (sometimes fatal), have been reported with minocycline use in the treatment of acne. Discontinue minocycline if liver injury is suspected.

5.6 Central Nervous System Effects

Central nervous system side effects including light-headedness, dizziness, or vertigo have been reported with minocycline therapy. Caution patients who experience these symptoms about driving vehicles or using hazardous machinery while on minocycline. These symptoms may disappear during therapy and usually rapidly disappear when minocycline is discontinued.

5.7 Idiopathic Intracranial Hypertension

Idiopathic intracranial hypertension has been associated with the use of tetracycline-class drugs, including minocycline. Clinical manifestations of idiopathic intracranial hypertension include headache, blurred vision, diplopia, and vision loss; papilledema can be found on fundoscopy. Women of childbearing age who are overweight or have a history of idiopathic intracranial hypertension are at a greater risk for developing idiopathic intracranial hypertension. Avoid concomitant use of isotretinoin and minocycline because isotretinoin, a systemic retinoid, is also known to cause idiopathic intracranial hypertension.

Permanent visual loss may exist, even after the medication is discontinued. If visual disturbance occurs during treatment, prompt ophthalmologic evaluation is warranted. Because intracranial pressure can remain elevated for weeks after drug cessation, monitor patients until they stabilize.

5.8 Autoimmune Syndromes

Tetracyclines have been associated with the development of autoimmune syndromes. The long-term use of minocycline in the treatment of acne has been associated with drug-induced lupus-like syndrome, autoimmune hepatitis, and vasculitis. Sporadic cases of serum sickness have presented shortly after minocycline use. Symptoms may be manifested by fever, rash, arthralgia, and malaise. Evaluate symptomatic patients. If symptoms occur, immediately discontinue use of minocycline.

5.9 Metabolic Effects

The anti-anabolic action of the tetracyclines, including minocycline, may cause an increase in blood urea nitrogen (BUN). In patients with significantly impaired renal function, higher serum levels of tetracycline-class drugs may lead to azotemia, hyperphosphatemia, and acidosis. If renal impairment exists, lower the total doses of minocycline, and if therapy is prolonged, monitor serum levels minocycline.

5.10 Photosensitivity

Photosensitivity manifested by an exaggerated sunburn reaction has been observed in some individuals taking tetracyclines, including minocycline. Advise patients to minimize or avoid exposure to natural or artificial sunlight (e.g., tanning beds or UVA/B treatment) while using minocycline. Instruct patients to use sunscreen products and wear protective apparel (e.g., hat) when exposure to sun cannot be avoided.

5.11 Tissue Hyperpigmentation

Tetracycline-class antibiotics are known to cause hyperpigmentation. Tetracycline therapy may induce hyperpigmentation in many organs, including nails, bone, skin, eyes, thyroid, visceral tissue, oral cavity (e.g., teeth, mucosa, alveolar bone), sclerae and heart valves. Skin and oral pigmentation has been reported to occur independently of time or amount of drug administration, whereas other tissue pigmentation has been reported to occur upon prolonged administration. Skin pigmentation includes diffuse pigmentation as well as over sites of scars or injury.

5.12 Development of Drug-Resistant Bacteria

Bacterial resistance to tetracyclines may develop in patients using minocycline hydrochloride extended-release tablets. Because of the potential for drug-resistant bacteria to develop during the use of minocycline hydrochloride extended-release tablets, it should be used only as indicated.

5.13 Superinfection

Use of minocycline hydrochloride extended-release tablets may result in overgrowth of non-susceptible organisms, including fungi. If superinfection occurs, discontinue minocycline hydrochloride extended-release tablets and institute appropriate therapy.

5.14 Laboratory Monitoring

Perform periodic laboratory evaluations of organ systems, including hematopoietic, renal, and hepatic studies.

6 ADVERSE REACTIONS

The following clinically significant adverse reactions are described elsewhere in the labeling:

- Serious Skin/Hypersensitivity Reactions [see Warnings and Precautions (5.1)]
- Clostridioides difficile-Associated Diarrhea (Antibiotic-Associated Colitis) [see Warnings and Precautions (5.4)]
- Hepatotoxicity [see Warnings and Precautions (5.5)]
- Central Nervous System Effects [see Warnings and Precautions (5.6)]
- Idiopathic Intracranial Hypertension [see Warnings and Precautions (5.7)]

6.1 Clinical Trials Experience

Because clinical trials are conducted under widely varying conditions, adverse reaction rates observed in the clinical trials of a drug cannot be directly compared to rates in the clinical trials of another drug, and may not reflect the rates observed in practice.

The following table summarizes selected adverse reactions reported in clinical trials at a rate of >1% for minocycline hydrochloride extended-release tablets and higher than placebo.

Adverse Reactions | Minocycline Hydrochloride Extended-Release Tablets (1 mg/kg) N = 674 (%) | PLACEBO N = 364 (%)
At least one treatment-emergent event | 379 (56) | 197 (54)
Fatigue | 62 (9) | 24 (7)
Dizziness | 59 (9) | 17 (5)
Pruritus | 31 (5) | 16 (4)
Malaise | 26 (4) | 9 (3)
Somnolence | 13 (2) | 3 (1)
Urticaria | 10 (2) | 1 (0)
Tinnitus | 10 (2) | 5 (1)
Arthralgia | 9 (1) | 2 (0)
Vertigo | 8 (1) | 3 (1)

6.2 Postmarketing Experience

The following adverse reactions have been reported with minocycline hydrochloride use in a variety of indications.

Because these reactions are reported voluntarily from a population of uncertain size, it is not always possible to reliably estimate their frequency or establish a causal relationship to drug exposure.

Skin and hypersensitivity reactions: anaphylaxis, angioedema, DRESS syndrome, erythema multiforme, Stevens-Johnson syndrome, acute febrile neutrophilic dermatosis (Sweet's syndrome), fixed drug eruptions, balanitis, anaphylactoid purpura, photosensitivity, pigmentation of skin and mucous membranes.

Autoimmune conditions: polyarthralgia, pericarditis, exacerbation of systemic lupus, pulmonary infiltrates with eosinophilia, lupus-like syndrome.

Central nervous system: idiopathic intracranial hypertension, bulging fontanels in infants, decreased hearing.

Endocrine: brown-black microscopic thyroid discoloration, abnormal thyroid function.

Oncology: thyroid cancer.

Oral: glossitis, dysphagia, tooth discoloration.

Gastrointestinal: enterocolitis, pancreatitis, hepatitis, liver failure.

Renal: acute renal failure.

Hematology: hemolytic anemia, thrombocytopenia, eosinophilia.

7 DRUG INTERACTIONS

7.1 Anticoagulants

Because tetracyclines have been shown to depress plasma prothrombin activity, patients who are on anticoagulant therapy may require downward adjustment of their anticoagulant dosage.

7.2 Penicillin

Because bacteriostatic drugs may interfere with the bactericidal action of penicillin, avoid giving minocycline hydrochloride in conjunction with penicillin.

7.3 Antacids and Iron Preparations

Absorption of tetracyclines is impaired by antacids containing aluminum, calcium, or magnesium and iron-containing preparations.

7.4 Drug/Laboratory Test Interactions

False elevations of urinary catecholamine levels may occur due to interference with the fluorescence test.

8 USE IN SPECIFIC POPULATIONS

8.1 Pregnancy

Risk Summary

Tetracycline class drugs, including minocycline may cause permanent discoloration of deciduous teeth and reversible inhibition of bone growth when administered during the second and third trimesters of pregnancy [see Warnings and Precautions (5.2, 5.3) and Use in Specific Populations (8.4)]. A few postmarketing cases of limb reductions have been reported over decades of use; however, the association is unclear. The limited data from postmarketing reports are not sufficient to inform a drug-associated risk for birth defects or miscarriage.

In animal reproduction studies conducted in pregnant rats and rabbits, fetuses with bent limb bones were observed following oral administration of minocycline during organogenesis at systemic exposures 3 and 2 times, respectively, the exposure associated with the maximum recommended human dose (MRHD) (see Data).

If a patient becomes pregnant while taking this drug, advise the patient of the risk to the fetus and to discontinue treatment.

The background risk of major birth defects and miscarriage for the indicated population is unknown. All pregnancies have a background risk of birth defect, loss, or other adverse outcomes. In the U.S. general population, the estimated background risk of major birth defects and miscarriage in clinically recognized pregnancies is 2 to 4% and 15 to 20%, respectively.

Data

Human Data

The use of tetracycline class drugs, including minocycline, during tooth development (second and third trimesters of pregnancy, infancy, and childhood up to the age of 8 years) may cause permanent discoloration of deciduous teeth (yellow-gray-brown). Permanent discoloration of the teeth is more common during long-term use of the drug but has been observed following repeated short-term courses [see Warnings and Precautions (5.2)].

Animal Data

Results of animal studies indicate that tetracyclines cross the placenta, are found in fetal tissues, and can cause delayed skeletal development in the developing fetus. Evidence of embryotoxicity has been noted in animals treated early in pregnancy [see Warnings and Precautions (5.3)].

Minocycline induced skeletal malformations (bent limb bones) in fetuses when administered to pregnant rats and rabbits during the period of organogenesis at doses of 30 mg/kg/day and 100 mg/kg/day, respectively (3 times the MRHD and 2 times the MRHD on an AUC comparison basis, respectively). Reduced mean fetal body weight was observed in studies in which minocycline was administered to pregnant rats at an oral dose of 10 mg/kg/day (approximately equal to the MRHD on an AUC comparison basis).

Minocycline was assessed for effects on peri- and post-natal development of rats in a study that involved oral administration to pregnant rats during the period of organogenesis through lactation at dosages of 5 mg/kg/day, 10 mg/kg/day, or 50 mg/kg/day. In this study, body weight gain was significantly reduced in pregnant females that received 50 mg/kg/day (2.5 times the MRHD on an AUC comparison basis). No effects of treatment on the duration of the gestation period or the number of live pups born per litter were observed. Gross external anomalies observed in offspring of animals that received minocycline included reduced body size, improperly rotated forelimbs, and reduced size of extremities. No effects were observed on the physical development, behavior, learning ability, or reproduction of the offspring of animals that received minocycline.

8.2 Lactation

Risk Summary

Tetracycline-class antibiotics, including minocycline, are present in breast milk following oral administration. There are no data on the effects of minocycline on milk production. Because of the potential for serious adverse reactions, including tooth discoloration and inhibition of bone growth, advise patients that breastfeeding is not recommended during minocycline therapy and for 4 days after the final dose [see Warnings and Precautions (5.2, 5.3)].

8.4 Pediatric Use

The safety and effectiveness of minocycline hydrochloride have been established in pediatric patients 12 years of age and older for the treatment of inflammatory lesions of non-nodular moderate to severe acne vulgaris [see Clinical Studies (14)]. Tooth discoloration and inhibition of bone growth have been observed in pediatric patients [see Warnings and Precaution (5.2, 5.3)]. Use of tetracycline-class antibiotics below the age of 8 is not recommended due to the potential for tooth discoloration [see Warnings and Precautions (5.2)].

Safety and effectiveness of minocycline have not been established in pediatric patients younger than 12 years of age.

8.5 Geriatric Use

Clinical studies of minocycline hydrochloride extended-release tablets did not include sufficient numbers of subjects aged 65 and over to determine whether they respond differently from younger subjects. Other reported clinical experience has not identified differences in responses between the elderly and younger patients. In general, dose selection for an elderly patient should be cautious, usually starting at the low end of the dosing range, reflecting the greater frequency of decreased hepatic, renal, or cardiac function, and concomitant disease or other drug therapy.

10 OVERDOSAGE

Minocycline is not removed in significant quantities by hemodialysis or peritoneal dialysis. In case of overdosage, discontinue minocycline, treat symptomatically, and institute supportive measures. Call Poison Control Center at 1-800 222-1222 for the latest recommendations.

11 DESCRIPTION

Minocycline hydrochloride, a semi synthetic derivative of tetracycline, is [4S-(4α,4aα,5aα,12aα)]-4,7-Bis(dimethylamino)-1,4,4a,5,5a,6,11,12a-octahydro-3,10, 12,12a-tetrahydroxy-1,11-dioxo-2-naphthacenecarboxamide mono hydrochloride. The structural formula is represented below:

C23H27N3O7•HCl M. W. 493.95

Each minocycline hydrochloride extended-release tablet, USP intended for oral administration contains minocycline hydrochloride equivalent to 45 mg, 55 mg, 65 mg, 80 mg, 90 mg, 105 mg, 115 mg or 135 mg of minocycline. In addition, each tablet contains the following inactive ingredients: colloidal silicon dioxide, hypromellose, lactose monohydrate, magnesium stearate, polyethylene glycol (55 mg, 65 mg, 80 mg, 90 mg, 105 mg, 115 mg and 135 mg only), titanium dioxide and triacetin.

Additionally, the 45 mg tablets contain ferric oxide black and ferric oxide yellow; the 55 mg tablets contain ferric oxide red and ferric oxide yellow; the 65 mg tablets contain FD & C blue #2 aluminum lake; the 80 mg tablets contain FD & C blue #2 aluminum lake and FD & C red #40 aluminum lake; the 90 mg tablets contain D & C yellow #10 aluminum lake, ferric oxide red and ferric oxide yellow; the 105 mg tablets contain FD & C blue #2 aluminum lake and FD & C red #40 aluminum lake; the 115 mg tablets contain FD & C blue #2 aluminum lake and ferric oxide yellow; the 135 mg tablets contain D & C red #27 aluminum lake, D & C yellow #10 aluminum lake and FD & C blue #2 aluminum lake.

USP dissolution test-8 used.

USP organic impurities procedure pending.

12 CLINICAL PHARMACOLOGY

12.1 Mechanism of Action

The mechanism of action of minocycline hydrochloride extended-release tablets for the treatment of acne is unknown.

12.2 Pharmacodynamics

The pharmacodynamics of minocycline hydrochloride extended-release tablets for the treatment of acne are unknown.

12.3 Pharmacokinetics

Minocycline hydrochloride extended-release tablets are not bioequivalent to non-modified release minocycline products. Based on pharmacokinetic studies in healthy adults, minocycline hydrochloride extended-release tablets produce a delayed Tmax at 3.5 hours to 4 hours as compared to a non-modified release reference minocycline product (Tmax at 2.25 hours to 3 hours). At steady-state (Day 6), the mean AUC(0 to 24) and Cmax were 33.32 mcg×hr/mL and 2.63 mcg/mL for minocycline hydrochloride extended-release tablets and 46.35 mcg×hr/mL and 2.92 mcg/mL for minocycline hydrochloride capsules, respectively. These parameters are based on dose adjusted to 135 mg/day for both products.

A single-dose, four-way crossover study demonstrated that minocycline hydrochloride extended-release tablets used in the study (45 mg, 90 mg, 135 mg) exhibited dose-proportional pharmacokinetics. In another single-dose, five-way crossover pharmacokinetic study, minocycline hydrochloride extended-release tablets 55 mg, 80 mg, and 105 mg were shown to be dose-proportional to minocycline hydrochloride extended-release tablets 90 mg and 135 mg.

When minocycline hydrochloride extended-release tablets were administered concomitantly with a meal that included dairy products, the extent and timing of absorption of minocycline did not differ from that of administration under fasting conditions.

Minocycline is lipid soluble and distributes into the skin and sebum.

13 NONCLINICAL TOXICOLOGY

13.1 Carcinogenesis, Mutagenesis, Impairment of Fertility

In a carcinogenicity study in which minocycline hydrochloride was orally administered to male and female rats once daily for up to 104 weeks at dosages up to 200 mg/kg/day, minocycline hydrochloride was associated in both sexes with follicular cell tumors of the thyroid gland, including increased incidences of adenomas, carcinomas and the combined incidence of adenomas and carcinomas in males, and adenomas and the combined incidence of adenomas and carcinomas in females. In a carcinogenicity study in which minocycline hydrochloride was orally administered to male and female mice once daily for up to 104 weeks at dosages up to 150 mg/kg/day, exposure to minocycline hydrochloride did not result in a significantly increased incidence of neoplasms in either males or females.

Minocycline was not mutagenic in vitro in a bacterial reverse mutation assay (Ames test) or CHO/HGPRT mammalian cell assay in the presence or absence of metabolic activation. Minocycline was not clastogenic in vitro using human peripheral blood lymphocytes or in vivo in a mouse micronucleus test.

Male and female reproductive performance in rats was unaffected by oral doses of minocycline of up to 300 mg/kg/day (40 times the MRHD on an AUC comparison basis). However, oral administration of 100 mg/kg/day or 300 mg/kg/day of minocycline to male rats (15 to 40 times the MRHD on an AUC comparison basis) adversely affected spermatogenesis. Effects observed at 300 mg/kg/day included a reduced number of sperm cells per gram of epididymis, an apparent reduction in the percentage of sperm that were motile, and (at 100 mg/kg/day and 300 mg/kg/day) increased numbers of morphologically abnormal sperm cells. Morphological abnormalities observed in sperm samples included absent heads, misshapen heads, and abnormal flagella.

14 CLINICAL STUDIES

The safety and efficacy of minocycline hydrochloride extended-release tablets in the treatment of inflammatory lesions of non-nodular moderate to severe acne vulgaris was assessed in two 12-week, multi-center, randomized, double-blind, placebo-controlled trials in adult and pediatric subjects 12 years of age and older (Trial 1 and Trial 2). A total of 924 subjects with non-nodular moderate to severe acne vulgaris received minocycline or placebo for a total of 12 weeks. The mean age of subjects was 20 years and subjects were from the following racial groups: White (73%), Hispanic (13%), Black (11%), Asian/Pacific Islander (2%), and Other (2%).

The two primary efficacy endpoints were:

1) Mean percent change in inflammatory lesion counts from Baseline to 12 weeks.

2) Percentage of subjects with an Evaluator's Global Severity Assessment (EGSA) of clear or almost clear at 12 weeks.

Efficacy results are presented in Table 4.

 | Trial 1 |  | Trial 2
 | Minocycline Hydrochloride Extended-Release Tablets (1 mg/kg) N = 300 | Placebo N = 151 | Minocycline Hydrochloride Extended-Release Tablets (1 mg/kg) N = 315 | Placebo N = 158
Mean Percent Improvement in Inflammatory Lesions | 43.1% | 31.7% | 45.8% | 30.8%
No. (%) of Subjects Clear or Almost Clear on the EGSA* | 52 (17.3%) | 12 (7.9%) | 50 (15.9%) | 15 (9.5%)

Minocycline hydrochloride extended-release tablets did not demonstrate any effect on non-inflammatory lesions (benefit or worsening).

16 HOW SUPPLIED/STORAGE AND HANDLING

How Supplied

Minocycline Hydrochloride Extended-release Tablets, USP 45 mg are grey colored, modified capsule shaped, biconvex, coated tablets, debossed with "531" on one side and plain on other side and are supplied as follows:

NDC 68382-531-06 in bottles of 30 tablets with child resistance closure

NDC 68382-531-16 in bottles of 90 tablets with child resistance closure

NDC 68382-531-01 in bottles of 100 tablets with child resistance closure

NDC 68382-531-05 in bottles of 500 tablets

NDC 68382-531-10 in bottles of 1000 tablets

NDC 68382-531-30 in unit-dose blister cartons of 100 (10 x 10) unit-dose tablets

Minocycline Hydrochloride Extended-release Tablets, USP 55 mg are yellow colored, modified capsule shaped, biconvex, coated tablets, debossed with "550" on one side and plain on other side and are supplied as follows:

NDC 68382-550-06 in bottles of 30 tablets with child resistance closure

NDC 68382-550-16 in bottles of 90 tablets with child resistance closure

NDC 68382-550-01 in bottles of 100 tablets with child resistance closure

NDC 68382-550-05 in bottles of 500 tablets

NDC 68382-550-10 in bottles of 1000 tablets

NDC 68382-550-30 in unit-dose blister cartons of 100 (10 x 10) unit-dose tablets

Minocycline Hydrochloride Extended-release Tablets, USP 65 mg are blue colored, modified capsule shaped, biconvex, coated tablets, debossed with "532" on one side and plain on other side and are supplied as follows:

NDC 68382-532-06 in bottles of 30 tablets with child resistance closure

NDC 68382-532-16 in bottles of 90 tablets with child resistance closure

NDC 68382-532-01 in bottles of 100 tablets with child resistance closure

NDC 68382-532-05 in bottles of 500 tablets

NDC 68382-532-10 in bottles of 1000 tablets

NDC 68382-532-30 in unit-dose blister cartons of 100 (10 x 10) unit-dose tablets

Minocycline Hydrochloride Extended-release Tablets, USP 80 mg are whitish blue colored, modified capsule shaped, biconvex, coated tablets, debossed with "551" on one side and plain on other side and are supplied as follows:

NDC 68382-551-06 in bottles of 30 tablets with child resistance closure

NDC 68382-551-16 in bottles of 90 tablets with child resistance closure

NDC 68382-551-01 in bottles of 100 tablets with child resistance closure

NDC 68382-551-05 in bottles of 500 tablets

NDC 68382-551-10 in bottles of 1000 tablets

NDC 68382-551-30 in unit-dose blister cartons of 100 (10 x 10) unit-dose tablets

Minocycline Hydrochloride Extended-release Tablets, USP 90 mg are light yellow colored, modified capsule shaped, biconvex, coated tablets, debossed with "533" on one side and plain on other side and are supplied as follows:

NDC 68382-533-06 in bottles of 30 tablets with child resistance closure

NDC 68382-533-16 in bottles of 90 tablets with child resistance closure

NDC 68382-533-01 in bottles of 100 tablets with child resistance closure

NDC 68382-533-05 in bottles of 500 tablets

NDC 68382-533-10 in bottles of 1000 tablets

NDC 68382-533-30 in unit-dose blister cartons of 100 (10 x 10) unit-dose tablets

Minocycline Hydrochloride Extended-release Tablets, USP 105 mg are light blue colored, modified capsule shaped, biconvex, coated tablets, debossed with "552" on one side and plain on other side and are supplied as follows:

NDC 68382-552-06 in bottles of 30 tablets with child resistance closure

NDC 68382-552-16 in bottles of 90 tablets with child resistance closure

NDC 68382-552-01 in bottles of 100 tablets with child resistance closure

NDC 68382-552-05 in bottles of 500 tablets

NDC 68382-552-10 in bottles of 1000 tablets

NDC 68382-552-30 in unit-dose blister cartons of 100 (10 x 10) unit-dose tablets

Minocycline Hydrochloride Extended-release Tablets, USP 115 mg are green colored, modified capsule shaped, biconvex, coated tablets, debossed with "534" on one side and plain on other side and are supplied as follows:

NDC 68382-534-06 in bottles of 30 tablets with child resistance closure

NDC 68382-534-16 in bottles of 90 tablets with child resistance closure

NDC 68382-534-01 in bottles of 100 tablets with child resistance closure

NDC 68382-534-05 in bottles of 500 tablets

NDC 68382-534-10 in bottles of 1000 tablets

NDC 68382-534-30 in unit-dose blister cartons of 100 (10 x 10) unit-dose tablets

Minocycline Hydrochloride Extended-release Tablets, USP 135 mg are light pink colored, modified capsule shaped, biconvex, coated tablets, debossed with "535" on one side and plain on other side and are supplied as follows:

NDC 68382-535-06 in bottles of 30 tablets with child resistance closure

NDC 68382-535-16 in bottles of 90 tablets with child resistance closure

NDC 68382-535-01 in bottles of 100 tablets with child resistance closure

NDC 68382-535-05 in bottles of 500 tablets

NDC 68382-535-10 in bottles of 1000 tablets

NDC 68382-535-30 in unit-dose blister cartons of 100 (10 x 10) unit-dose tablets

Storage

Store at 20° to 25°C (68° to 77°F) [See USP Controlled Room Temperature].

Handling

Keep this and all drugs out of the reach of children.

Protect from light, moisture and excessive heat.

Dispense in a tight, light-resistant container as defined in the USP with child-resistant closure.

17 PATIENT COUNSELING INFORMATION

Advise the patient to read the FDA-approved patient labeling (Patient Information).

Patients taking minocycline hydrochloride extended-release tablets should receive the following information and instructions:

Administration Instructions

- Minocycline hydrochloride extended-release tablets should be taken exactly as directed.
- Advise patients to swallow minocycline extended-release tablets whole and not to chew, crush, or split the tablets [see Dosage and Administration (2)].

Serious Skin/Hypersensitivity Reactions

- Inform patients that serious skin reactions have occurred with the minocycline use in patients with acne. Advise patients to discontinue use of minocycline extended-release tablets and contact their healthcare provider immediately at the first evidence of skin erythema [see Warnings and Precautions (5.1)].

Tooth Discoloration and Enamel Hypoplasia

- Advise patients that minocycline extended-release tablets use in pregnancy may cause permanent tooth discoloration of deciduous teeth. Advise patients to discontinue minocycline extended-release tablets during pregnancy and to inform their healthcare provider right away if they become pregnant during treatment [see Warnings and Precautions (5.2), Use in Specific Populations (8.1)].
- Advise caregivers of pediatric patients that minocycline extended-release tablets use may cause permanent discoloration of deciduous and permanent teeth [see Warnings and Precautions (5.2), Use in Specific Populations (8.4)].

Inhibition of Bone Growth

- Advise patients that minocycline use in pregnancy may cause inhibition of fetal bone growth. Advise patients to discontinue minocycline during pregnancy and to inform their healthcare provider right away if they become pregnant during treatment [see Warnings and Precautions (5.3), Use in Specific Populations (8.1)].

Clostridioides difficile-Associated Diarrhea (Antibiotic-Associated Colitis)

- Advise patients that Clostridioides difficile-associated diarrhea (antibiotic-associated colitis) can occur with minocycline therapy, including minocycline extended-release tablets. If patients develop watery or bloody stools, advise patients to seek medical attention [see Warnings and Precautions (5.4)].

Hepatotoxicity

- Inform patients about the possibility of hepatotoxicity. Advise patients to seek medical advice if they experience signs or symptoms of hepatotoxicity, including loss of appetite, tiredness, diarrhea, jaundice, bleeding easily, confusion, and sleepiness [see Warnings and Precautions (5.5)].

Central Nervous System Effects

- Inform patients that central nervous system adverse reactions including dizziness or vertigo have been reported with oral minocycline therapy. Caution patients about driving vehicles or using hazardous machinery if they experience such symptoms while on minocycline[see Warnings and Precautions (5.6)].

Idiopathic Intracranial Hypertension

- Inform patients that idiopathic intracranial hypertension can occur with minocycline therapy. Advise patients to seek medical attention if they develop unusual headache, visual symptoms, such as blurred vision, diplopia, and vision loss [see Warnings and Precautions (5.7)].

Autoimmune Syndromes

- Inform patients that autoimmune syndromes, including drug-induced lupus-like syndrome, autoimmune hepatitis, vasculitis, and serum sickness have been observed with tetracycline-class drugs, including minocycline. Symptoms may be manifested by arthralgia, fever, rash, and malaise. Advise patients who experience such symptoms to immediately discontinue minocycline and seek medical help [see Warnings and Precautions (5.8)].

Photosensitivity

- Inform patients that photosensitivity manifested by an exaggerated sunburn reaction has been observed in some individuals taking tetracyclines, including minocycline. Advise patients to minimize or avoid exposure to natural or artificial sunlight (i.e., tanning beds or UVA/B treatment) while using minocycline. Instruct patients to use sunscreen and wear protective clothing (e.g., hat) over treated areas when exposure to sun cannot be avoided [see Warnings and Precautions (5.10)].

Tissue Hyperpigmentation

- Inform patients that minocycline may cause discoloration of skin, scars, teeth, or gums [see Warnings and Precautions (5.11)].

Lactation

- Advise patients that minocycline therapy is not recommended during breast feeding for 4 days after the final dose [see Use in Specific Populations (8.2)].

Call your doctor for medical advice about side effects. You may report side effects to FDA at 1-800-FDA-1088.

Manufactured by:

Zydus Lifesciences Ltd.,

Ahmedabad, India

Distributed by:

Zydus Pharmaceuticals (USA) Inc.

Pennington, NJ 08534

Rev.: 06/25

Patient Information

Minocycline Hydrochloride Extended-release Tablets

What are minocycline hydrochloride extended-release tablets?

Minocycline hydrochloride extended-release tablets are a prescription medicine used to treat pimples and red bumps (non-nodular inflammatory lesions) that happen with moderate to severe acne vulgaris in people 12 years of age and older. Minocycline hydrochloride extended-release tablets are not effective for acne that is not red-looking (not-inflammatory acne).

- safe and effective for the treatment of infections.
- safe and effective in children under 12 years of age.

Who should not take minocycline hydrochloride extended-release tablets?

Do not take minocycline hydrochloride extended-release tablets if you are allergic to any tetracycline medicines. Ask your healthcare provider or pharmacist for a list of these medicines if you are not sure.

Before taking minocycline hydrochloride extended-release tablets, tell your healthcare provider about all of your medical conditions, including if you:

- have kidney problems.
- have liver problems.
- have diarrhea or watery stools.
- have had increased pressure around your brain that may have caused vision problems.
- are pregnant or plan to become pregnant. Minocycline hydrochloride extended-release tablets may harm your unborn baby. Taking minocycline hydrochloride extended-release tablets while you are pregnant may cause serious side effects on the growth of bone and teeth of your baby. Stop taking minocycline hydrochloride extended-release tablets and call your healthcare provider right away if you become pregnant during treatment with minocycline hydrochloride extended-release tablets.
- are breastfeeding or plan to breastfeed. Minocycline hydrochloride passes into your breast milk and may harm your baby. Do not breastfeed during treatment with minocycline hydrochloride extended-release tablets and for 4 days after your final dose.

Tell your healthcare provider about all the other medicines you take, including prescription and over-the-counter medicines, vitamins, and herbal supplements.

Minocycline hydrochloride extended-release tablets and other medicines may affect each other and can cause serious side effects. Minocycline may affect the way other medicines work, and other medicines may affect how Minocycline hydrochloride extended-release tablets works.

Especially tell your healthcare provider if you take:

- a blood thinner medicine.
- a penicillin antibiotic medicine.
- antacids that contain aluminum, calcium, or magnesium or iron-containing medicines.
- an acne medicine that contains isotretinoin

Ask your healthcare provider or pharmacist if you are not sure if your medicine is one that is listed above. Know the medicines you take. Keep a list of them to show your healthcare provider and pharmacist.

How should I take minocycline hydrochloride extended-release tablets?

- Take minocycline hydrochloride extended-release tablets exactly as your healthcare provider tells you.
- Take minocycline hydrochloride extended-release tablets 1 time per day with or without food. Taking minocycline hydrochloride extended-release tablets with food may lower your chances of getting irritation or ulcers in your esophagus. Your esophagus is the tube that connects your mouth to your stomach.
- Swallow minocycline hydrochloride extended-release tablets whole. Do not chew, crush, or split the tablets.

If you take too much minocycline hydrochloride extended-release tablets, stop taking minocycline hydrochloride extended-release tablet and call your healthcare provider or go to the nearest hospital emergency room, or contact a poison control center right away at 1-800-222-1222.

What should I avoid while taking minocycline hydrochloride extended-release tablets?

- You should not drive or operate dangerous machinery until you know how minocycline hydrochloride extended-release tablet affects you. Minocycline hydrochloride extended-release tablets may cause you to feel dizzy or lightheaded, or have a spinning feeling (vertigo).
- Avoid sunlight or artificial sunlight, such as sunlamps and tanning beds during treatment with minocycline hydrochloride extended-release tablet. Minocycline hydrochloride extended-release tablet can make your skin sensitive to the sun and artificial sunlight and you could get severe sunburn during treatment. Use sunscreen and wear a hat and protective clothing that covers your skin while out in the sunlight during treatment with minocycline hydrochloride extended-release tablet.

What are possible side effects of minocycline hydrochloride extended-release tablets?

Minocycline hydrochloride extended-release tablets may cause serious side effects, including:

- Serious skin and allergic reactions have happened during treatment with minocycline. Minocycline hydrochloride extended-release tablets may cause serious skin or allergic reactions that may also affect parts of your body such as your liver, lungs, kidneys, and heart. Sometimes these reactions can lead to death. Stop taking minocycline hydrochloride extended-release tablets and call your healthcare provider right away or go to the nearest hospital emergency room if you have any of the following signs or symptoms, including:

○ | skin redness, rash, hives, sores in your mouth, or your skin blisters and peels
○ | swelling of your face, eyes, lips, tongue, or throat
○ | trouble swallowing or breathing
○ | blood in your urine
○ | fever, yellowing of the skin or the whites of your eyes (jaundice), dark colored urine
○ | pain on the right side of the stomach area (abdominal pain)
○ | chest pain or abnormal heartbeats
○ | swelling in your legs, ankles, and feet

- Permanent tooth discoloration and problems with tooth enamel. Minocycline hydrochloride extended-release tablets may permanently turn a baby or child's teeth yellow-grey-brown during tooth development. Minocycline hydrochloride extended-release tablets may also cause tooth enamel to not develop properly. You should not use minocycline hydrochloride extended-release tablets during tooth development. Tooth development happens in the second and third trimesters of pregnancy, and in children from birth to 8 years of age. See "What should I tell my healthcare provider before taking minocycline hydrochloride extended-release tablets?"
- Slow bone growth. Minocycline hydrochloride extended-release tablets may cause slow bone growth if it is used during the second and third trimesters of pregnancy and if it is used in infants and children up to 8 years of age. Slow bone growth is reversible after stopping treatment with minocycline hydrochloride extended-release tablets.
- Diarrhea (antibiotic associated colitis). Antibiotic associated colitis can happen with most antibiotics, including minocycline hydrochloride extended-release tablets. This type of diarrhea may be caused by an infection (Clostridioides difficile) in your intestines and can be severe and can lead to death. Call your healthcare provider right away if you get watery diarrhea, diarrhea that does not go away, or bloody stools.
- Liver problems. Minocycline hydrochloride extended-release tablets may cause serious liver problems that can lead to death. Stop taking minocycline hydrochloride extended-release tablets and call your healthcare provider right away if you get any of the following symptoms of liver problems:

○ | loss of appetite
○ | tiredness
○ | diarrhea
○ | yellowing of your skin or the whites of your eyes (jaundice)
○ | unexplained bleeding or bleeding more easily than normal
○ | confusion
○ | sleepiness

- Central nervous system effects. See "What should I avoid while taking minocycline hydrochloride extended-release tablets?" Central nervous system effects such as light-headedness, dizziness, and a spinning feeling (vertigo) may go away during your treatment with minocycline hydrochloride extended-release tablets or if treatment is stopped.
- Increased pressure around the brain (idiopathic intracranial hypertension). This condition may lead to vision changes and permanent vision loss. You are more likely to get intracranial hypertension if you are a female who can have children, are overweight, and have already had intracranial hypertension. Stop taking minocycline hydrochloride extended-release tablets and tell your healthcare provider right away if you have blurred vision, double vision, vision loss, or unusual headaches.
- Immune system reactions including a lupus-like syndrome, hepatitis, and inflammationof blood or lymph vessels (vasculitis).Using minocycline hydrochloride extended-release tablets for a long time to treat acne may cause immune system reactions. Stop taking m inocycline hydrochloride extended-release tablets and tell your healthcare provider right away if you get a fever, rash, joint pain, or body weakness.
- Sensitivity to sunlight (photosensitivity). See"What should I avoid while taking minocycline hydrochloride extended-release tablets?"
- Discoloration (tissue hyperpigmentation). Minocycline hydrochloride extended-release tablets may cause darkening of your nails, skin, eyes, teeth, gums, scars, and internal organs.

The most common side effects of minocycline hydrochloride extended-release tablets include:

- headache
- tiredness
- dizziness or spinning feeling
- itching

Your healthcare provider may do blood tests and check you for side effects during treatment with minocycline hydrochloride extended-release tablets and may lower your dose or stop treatment if you develop certain side effects.

These are not all of the possible side effects of minocycline hydrochloride extended-release tablets.

Call your doctor for medical advice about side effects. You may report side effects to FDA at 1-800-FDA-1088. You may also report side effects to MedicalAffairs@ zydususa.com at 1-877-993-8779.

How should I store minocycline hydrochloride extended-release tablets?

- Store minocycline hydrochloride extended-release tablets between 59ºF to 86ºF (15ºC to 30ºC).
- Keep minocycline hydrochloride extended-release tablets in the container that it comes in and keep the container tightly closed.
- Keep minocycline hydrochloride extended-release tablets dry.

Keep minocycline hydrochloride extended-release tablets and all medicines out of the reach of children.

General information about the safe and effective use of minocycline hydrochloride extended-release tablets

Medicines are sometimes prescribed for purposes other than those listed in the Patient Information leaflet. Do not use minocycline hydrochloride extended-release tablets for a condition for which it was not prescribed. Do not give minocycline hydrochloride extended-release tablets to other people, even if they have the same symptoms you have. It may harm them. You can ask your pharmacist or healthcare provider for information about minocycline hydrochloride extended-release tablets that is written for health professionals.

Please address medical inquiries to, (MedicalAffairs@zydususa.com) Tel.: 1-877-993-8779.

What are the ingredients in minocycline hydrochloride extended-release tablets?

Active ingredient: minocycline hydrochloride, USP

Inactive ingredients: colloidal silicon dioxide, hypromellose, lactose monohydrate, magnesium stearate, polyethylene glycol (55 mg, 65 mg, 80 mg, 90 mg, 105 mg, 115 mg and 135 mg only), titanium dioxide and triacetin.

Additionally, the 45 mg tablets contain ferric oxide black and ferric oxide yellow; the 55 mg tablets contain ferric oxide red and ferric oxide yellow; the 65 mg tablets contain FD & C blue #2 aluminum lake; the 80 mg tablets contain FD & C blue #2 aluminum lake and FD & C red #40 aluminum lake; the 90 mg tablets contain D & C yellow #10 aluminum lake, ferric oxide red and ferric oxide yellow; the 105 mg tablets contain FD & C blue #2 aluminum lake and FD & C red #40 aluminum lake; the 115 mg tablets contain FD & C blue #2 aluminum lake and ferric oxide yellow; the 135 mg tablets contain D & C red #27 aluminum lake, D & C yellow #10 aluminum lake and FD & C blue #2 aluminum lake.

Brands mentioned are trademarks of their respective owners.

Manufactured by:

Zydus Lifesciences Ltd.,

Ahmedabad, India

Distributed by:

Zydus Pharmaceuticals (USA) Inc.

Pennington, NJ 08534

This Patient Information has been approved by the U.S. Food and Drug Administration

Rev.: 06/25

PACKAGE LABEL.PRINCIPAL DISPLAY PANEL

NDC 68382-531-01 in bottle of 100 Tablets

Minocycline Hydrochloride Extended-release Tablets, USP 45 mg

Rx only

100 TABLETS

ZYDUS

NDC 68382-550-01 in bottle of 100 Tablets

Minocycline Hydrochloride Extended-release Tablets, USP 55 mg

Rx only

100 TABLETS

ZYDUS

NDC 68382-532-01 in bottle of 100 Tablets

Minocycline Hydrochloride Extended-release Tablets, USP 65 mg

Rx only

100 TABLETS

ZYDUS

NDC 68382-551-01 in bottle of 100 Tablets

Minocycline Hydrochloride Extended-release Tablets, USP 80 mg

Rx only

100 TABLETS

ZYDUS

NDC 68382-533-01 in bottle of 100 Tablets

Minocycline Hydrochloride Extended-release Tablets, USP 90 mg

Rx only

100 TABLETS

ZYDUS

NDC 68382-552-01 in bottle of 100 Tablets

Minocycline Hydrochloride Extended-release Tablets, USP 105 mg

Rx only

100 TABLETS

ZYDUS

NDC 68382-534-01 in bottle of 100 Tablets

Minocycline Hydrochloride Extended-release Tablets, USP 115 mg

Rx only

100 TABLETS

ZYDUS

NDC 68382-535-01 in bottle of 100 Tablets

Minocycline Hydrochloride Extended-release Tablets, USP 135 mg

Rx only

100 TABLETS

ZYDUS